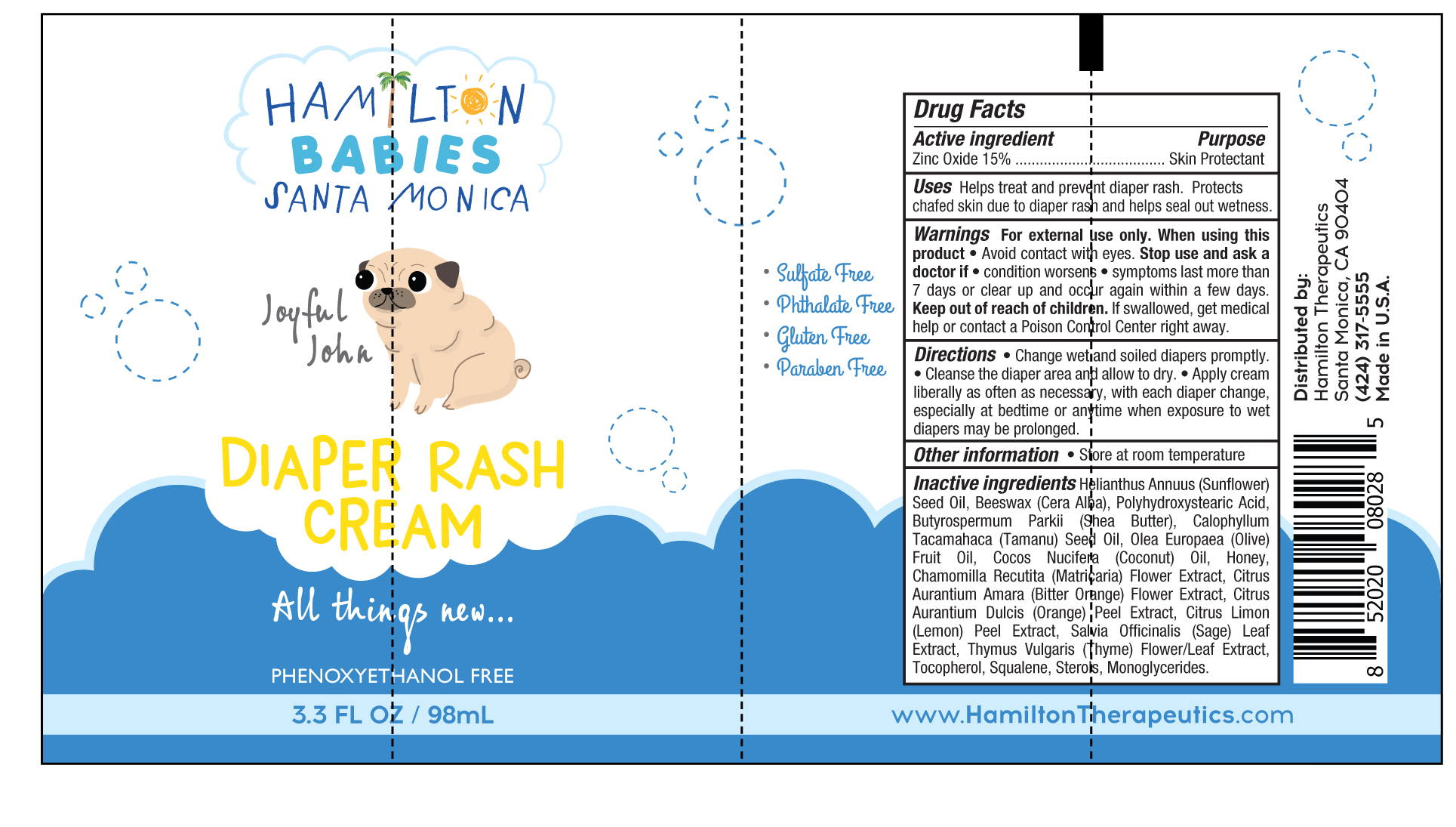 DRUG LABEL: Diaper Rash Cream
NDC: 72381-101 | Form: CREAM
Manufacturer: Hamilton Therapeutics, Inc
Category: otc | Type: HUMAN OTC DRUG LABEL
Date: 20221130

ACTIVE INGREDIENTS: ZINC OXIDE 15 g/100 mL
INACTIVE INGREDIENTS: SUNFLOWER OIL; POLYHYDROXYSTEARIC ACID (2300 MW); SHEA BUTTER; COCONUT OIL; CALOPHYLLUM TACAMAHACA SEED OIL; OLIVE OIL; HONEY; LEMON PEEL; SAGE; SQUALENE; WHITE WAX; CHAMOMILE; CITRUS AURANTIUM FLOWER; CITRUS SINENSIS FLOWER; THYME; TOCOPHEROL

Diaper Rash Cream

Active ingredient Purpose
Zinc Oxide 15% ..................................... Skin Protectant

PURPOSE

Uses Helps treat and prevent diaper rash. Protects
chafed skin due to diaper rash and helps seal out wetness.

Keep out of reach of children. If swallowed, get medical help or contact a Poison Control Center right away.

Stop use and ask adoctor if

• condition worsens

• symptoms last more than 7 days or clear up and occur again within a few days.

Warnings For external use only.

When using this product • Avoid contact with eyes

Directions

• Change wet and soiled diapers promptly.
• Cleanse the diaper area and allow to dry. • Apply cream liberally as often as necessary, with each diaper change,
especially at bedtime or anytime when exposure to wet diapers may be prolonged.

INACTIVE INGREDIENT

Inactive ingredients Helianthus Annuus (Sunflower) Seed Oil, Beeswax (Cera Alba), Polyhydroxystearic Acid, Butyrospermum Parkii (Shea Butter), Calophyllum Tacamahaca (Tamanu) Seed Oil, Olea Europaea (Olive) Fruit Oil, Cocos Nucifera (Coconut) Oil, Honey, Chamomilla Recutita (Matricaria) Flower Extract, Citrus Aurantium Amara (Bitter Orange) Flower Extract, Citrus Aurantium Dulcis (Orange) Peel Extract, Citrus Limon (Lemon) Peel Extract, Salvia Officinalis (Sage) Leaf Extract, Thymus Vulgaris (Thyme) Flower/Leaf Extract,Tocopherol, Squalene, Sterols, Monoglycerides.

PACKAGE LABEL

Diaper Rash Cream

3.3 FL OZ / 98mL